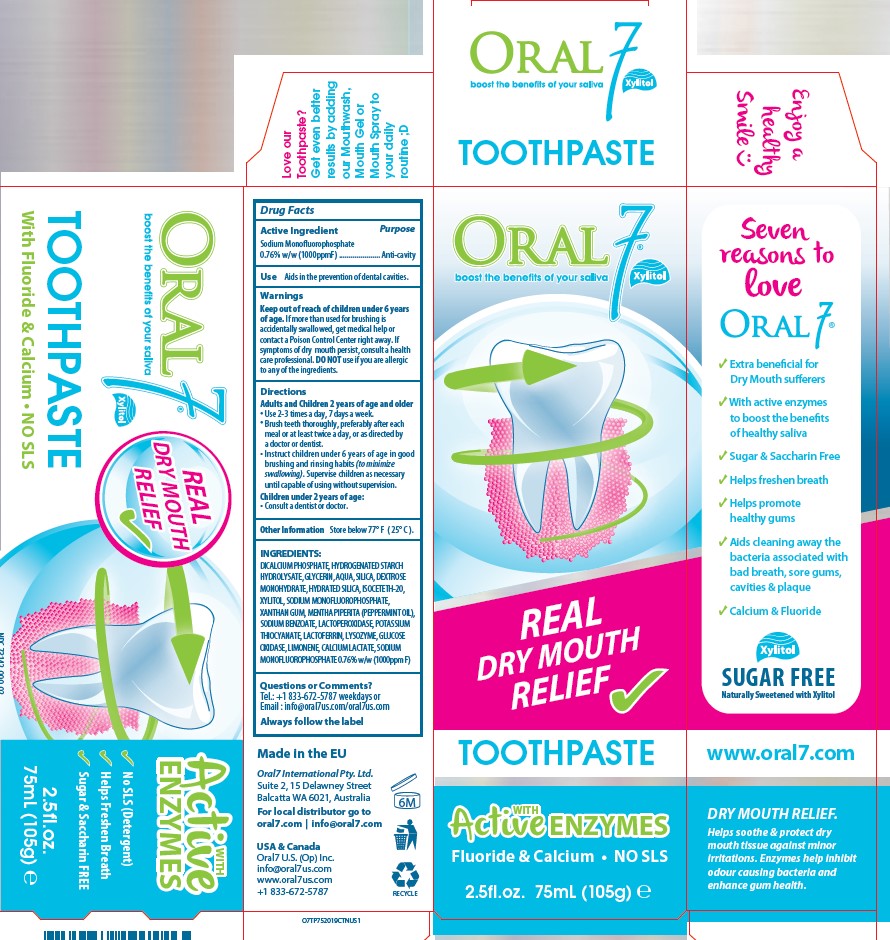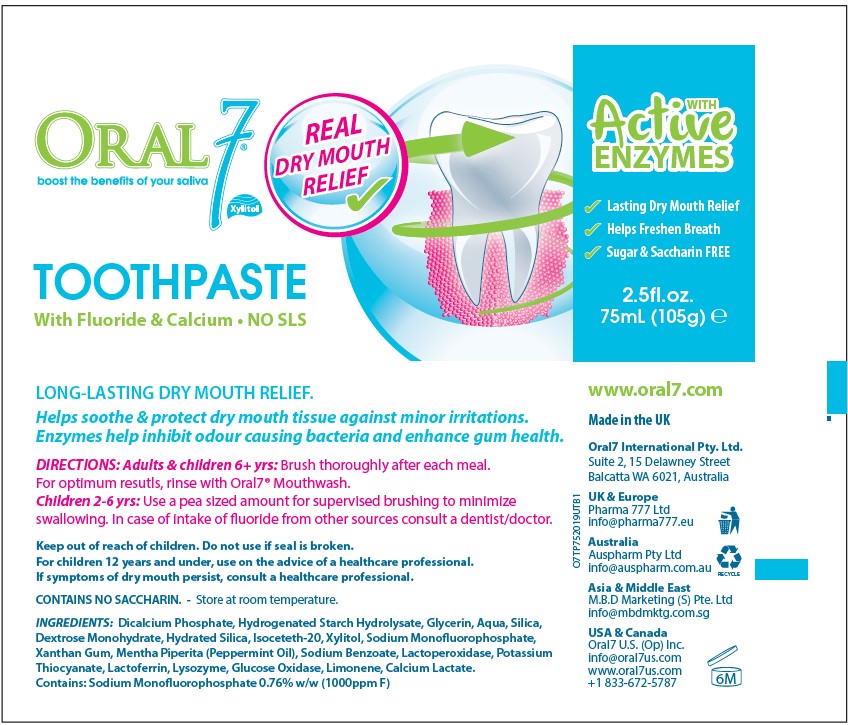 DRUG LABEL: Oral7 Dry Mouth Moisturizing
NDC: 81175-000 | Form: PASTE, DENTIFRICE
Manufacturer: Oral7 USA Operations Inc
Category: otc | Type: HUMAN OTC DRUG LABEL
Date: 20210614

ACTIVE INGREDIENTS: SODIUM MONOFLUOROPHOSPHATE 7.6 mg/1 mL
INACTIVE INGREDIENTS: XANTHAN GUM; LACTOFERRIN, BOVINE; LIMONENE, (+)-; HYDROGENATED STARCH HYDROLYSATE; ANHYDROUS DIBASIC CALCIUM PHOSPHATE; GLYCERIN; HYDRATED SILICA; DEXTROSE MONOHYDRATE; SILICON DIOXIDE; ISOCETETH-20; XYLITOL; WATER; SODIUM BENZOATE; MYELOPEROXIDASE; MENTHA PIPERITA; POTASSIUM THIOCYANATE; LYSOZYME; GLUCOSE OXIDASE; CALCIUM LACTATE

Oral7 Dry Mouth Moisturizing Toothpaste

Active Ingredient

Sodium Monofluorophosphate 0.76% w/w (1000ppmF)

Purpose

Anti-cavity

Use

Aids in the prevention of dental cavities.

Warnings

Keep out of reach of children

under 6 years of age. If more than used for brushing is accidentally swallowed, get medical help or contact a Poison Control Center right away. If symptoms of dry mouth persist, consult a health care professional.

DO NOT use

if you are allergic to any of the ingredients.

Directions

Adults and Children 2 years of age and older

- Use 2-3 times a day, 7 days a week.
- Brush teeth thoroughly, preferably after each meal or at least twice a day, or as directed by a doctor or dentist.
- Instruct children under 6 years of age in good brushing and rinsing habits (to minimize swallowing). Supervise children as necessary until capable of using without supervision.
  Children under 2 years of age: Consult a dentist or doctor.

Other Information

Store below 77° F (25° C).

Inactive ingredients

DICALCIUM PHOSPHATE, HYDROGENATED STARCH HYDROLYSATE, GLYCERIN, AQUA, SILICA, DEXTROSE MONOHYDRATE, HYDRATED SILICA, ISOCETETH-20, XYLITOL, SODIUM MONOFLUOROPHOSPHATE, XANTHAN GUM, MENTHA PIPERITA (PEPPERMINT OIL), SODIUM BENZOATE, LACTOPEROXIDASE, POTASSIUM THIOCYANATE, LACTOFERRIN, LYSOZYME, GLUCOSE OXIDASE, LIMONENE, CALCIUM LACTATE

Questions

or Comments? Tel.: +1 833-672-5787 weekdays or Email : info@oral7us.com / oral7us.com

Always follow the label

ORAL7

REAL DRY MOUTH RELIEF

TOOTHPASTE

Fluoride & Calcium

2.5 fl oz 75 ml (105g)

SUGAR FREE

Naturally Sweetened with Xylitol

Made in the EU

Oral7 International Pty. Ltd.

Suite 2, 15 Delawney Street

Balcatta, WA 6021 AUSTRALIA

USA & Canada

Oral7 U.S. (Op) Inc.info@oral7us.com

www.oral7us.com